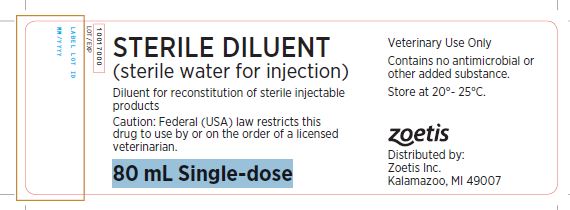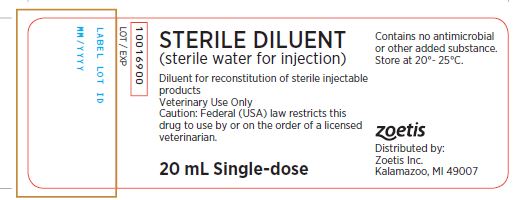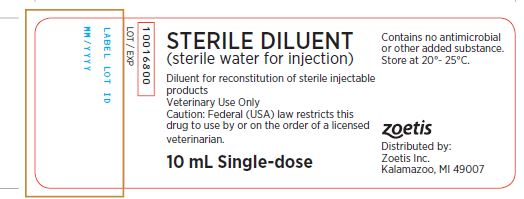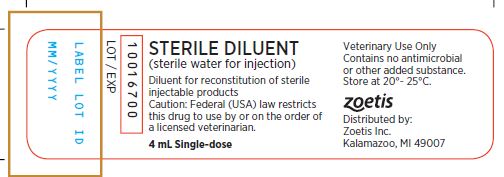 DRUG LABEL: Sterile Water
NDC: 54771-1060 | Form: INJECTION
Manufacturer: Zoetis Inc.
Category: animal | Type: PRESCRIPTION ANIMAL DRUG LABEL
Date: 20170210

ACTIVE INGREDIENTS: WATER 1 mL/1 mL

STERILE DILUENT(sterile water for injection)

PRECAUTIONS

Diluent for reconstitution of sterile injectable products

CAUTION:

Federal (USA) law restricts this drug to use by or on the order of a licensed

veterinarian.

Veterinary Use Only

CONTAINS:

Contains no antimicrobial or other added substance.

Store at 20°- 25°C.

No title

Distributed by:

Zoetis Inc.

Kalamazoo, MI 49007

Package Label - 80 mL label

STERILE DILUENT

(sterile water for injection)

Package Label - 20 mL Label

STERILE DILUENT

(sterile water for injection)

Package Label - 10 mL Label

STERILE DILUENT

(sterile water for injection)

Package Label - 4 mL label

STERILE DILUENT

(sterile water for injection)